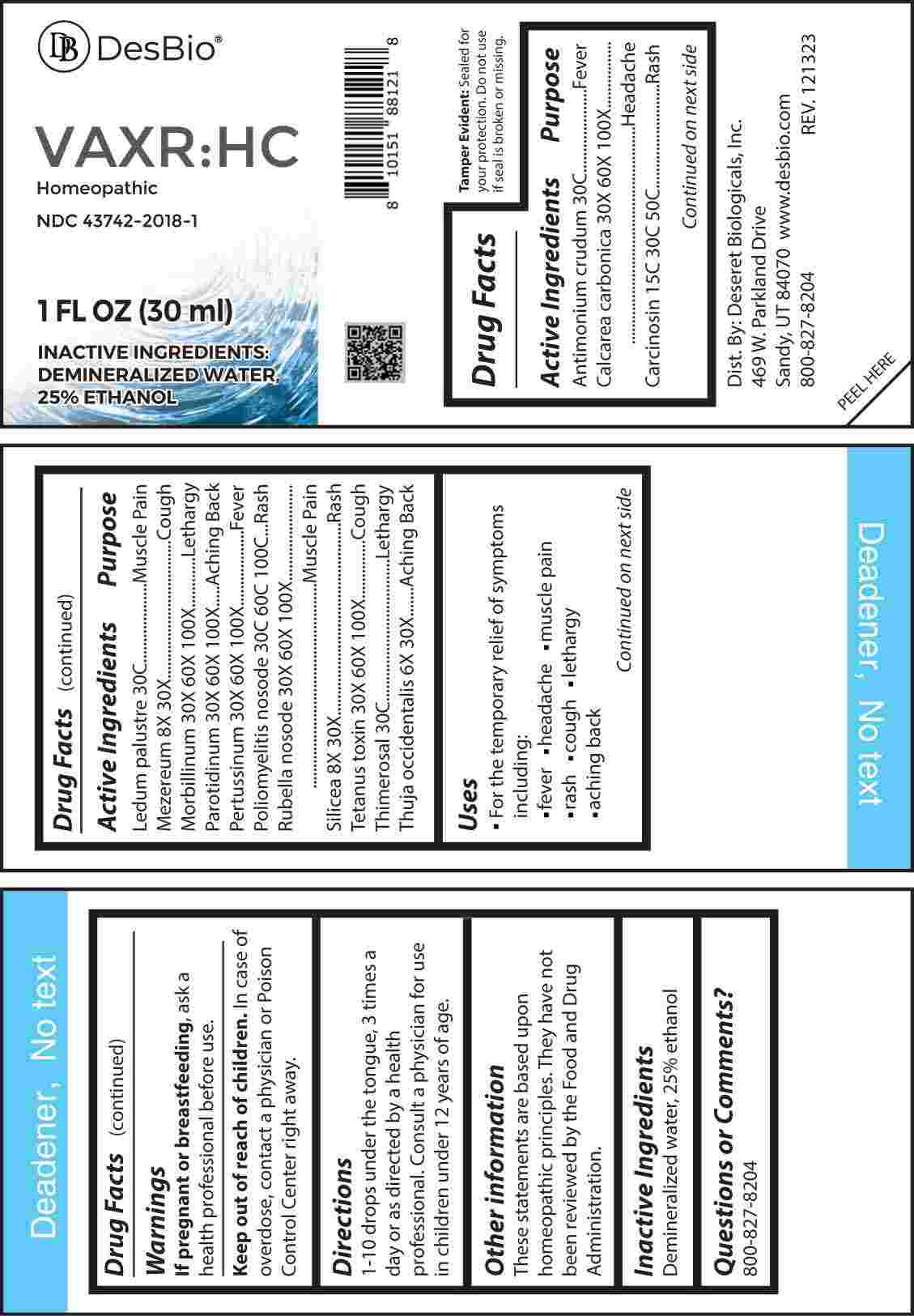 DRUG LABEL: VAXR HC
NDC: 43742-2018 | Form: LIQUID
Manufacturer: Deseret Biologicals, Inc.
Category: homeopathic | Type: HUMAN OTC DRUG LABEL
Date: 20240403

ACTIVE INGREDIENTS: THUJA OCCIDENTALIS LEAFY TWIG 6 [hp_X]/1 mL; DAPHNE MEZEREUM BARK 8 [hp_X]/1 mL; SILICON DIOXIDE 8 [hp_X]/1 mL; OYSTER SHELL CALCIUM CARBONATE, CRUDE 30 [hp_X]/1 mL; MEASLES VIRUS 30 [hp_X]/1 mL; MUMPS VIRUS 30 [hp_X]/1 mL; BORDETELLA PERTUSSIS 30 [hp_X]/1 mL; RUBELLA VIRUS 30 [hp_X]/1 mL; CLOSTRIDIUM TETANI 30 [hp_X]/1 mL; HUMAN BREAST TUMOR CELL 15 [hp_C]/1 mL; ANTIMONY TRISULFIDE 30 [hp_C]/1 mL; LEDUM PALUSTRE TWIG 30 [hp_C]/1 mL; THIMEROSAL 30 [hp_C]/1 mL; POLIOVIRUS 30 [hp_C]/1 mL
INACTIVE INGREDIENTS: WATER; ALCOHOL

DRUG FACTS:

ACTIVE INGREDIENTS:

Antimonium Crudum 30C, Calcarea Carbonica 30X, 60X, 100X, Carcinosin 15C, 30C, 50C, Ledum Palustre 30C, Mezereum 8X, 30X, Morbillinum 30X, 60X, 100X, Parotidinum 30X, 60X, 100X, Pertussinum 30X, 60X, 100X, Poliomyelitis Nosode 30C, 60C, 100C, Rubella Nosode 30X, 60X, 100X, Silicea 8X, 30X, Tetanus Toxin 30X, 60X, 100X, Thimerosal 30C, Thuja Occidentalis 6X, 30X.

PURPOSE:

Antimonium Crudum - Fever, Calcarea Carbonica - Headache, Carcinosin - Rash, Ledum Palustre – Muscle Pain, Mezereum - Cough, Morbillinum - Lethargy, Parotidinum – Aching Back, Pertussinum - Fever, Poliomyelitis Nosode - Rash, Rubella Nosode – Muscle Pain, Silicea - Rash, Tetanus Toxin - Cough, Thimerosal - Lethargy, Thuja Occidentalis – Aching Back

USES:

• For the temporary relief of symptoms including:

• fever • headache • muscle pain • rash

• cough • lethargy • aching back

These statements are based upon homeopathic principles. They have not been reviewed by the Food and Drug Administration.

WARNINGS:

If pregnant or breast-feeding, ask a health professional before use.

Keep out of reach of children. In case of overdose, contact a physician or Poison Control Center right away.

Tamper Evident: Sealed for your protection. Do not use if seal is broken or missing.

KEEP OUT OF REACH OF CHILDREN:

In case of overdose, contact a physician or Poison Control Center right away.

DIRECTIONS:

1-10 drops under the tongue, 3 times a day or as directed by a health professional. Consult a physician for use in children under 12 years of age.

INACTIVE INGREDIENTS:

Demineralized water, 25% ethanol

QUESTIONS:

Dist. By: Deseret Biologicals, Inc.

469 W. Parkland Drive

Sandy, UT 84070

www.desbio.com

800-827-8204

PACKAGE LABEL DISPLAY:

Des Bio

VAXR:HC

Homeopathic

NDC 43742-2018-1

1 FL OZ (30 ml)